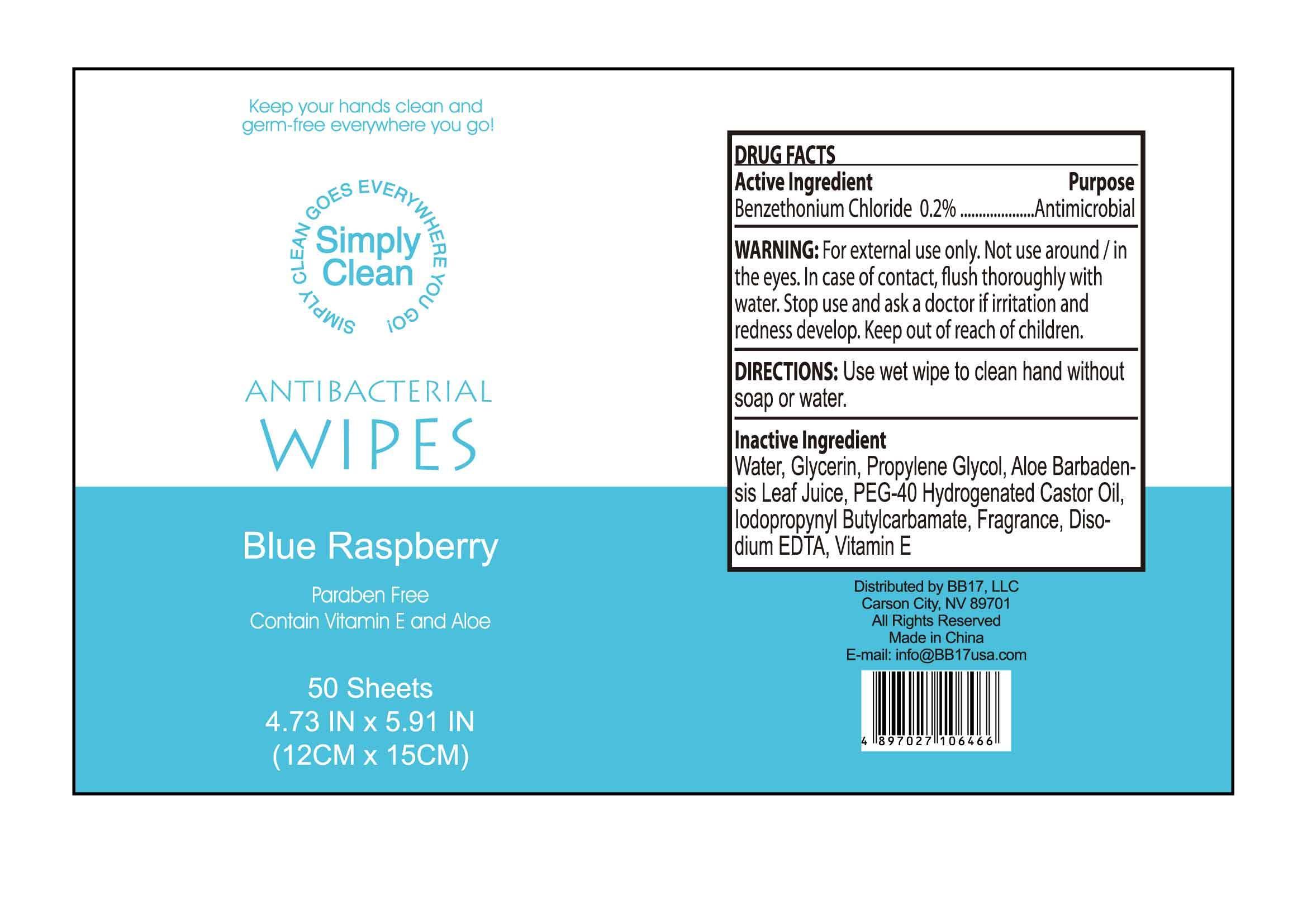 DRUG LABEL: ANTIBACTERIAL WIPES Blue Raspberry
NDC: 53603-3003 | Form: SWAB
Manufacturer: BB17, LLC
Category: otc | Type: HUMAN OTC DRUG LABEL
Date: 20121206

ACTIVE INGREDIENTS: BENZETHONIUM CHLORIDE 0.2 g/100 g
INACTIVE INGREDIENTS: WATER; ALOE; ALOE VERA LEAF; GLYCERIN; PROPYLENE GLYCOL; POLYOXYL 40 HYDROGENATED CASTOR OIL; IODOPROPYNYL BUTYLCARBAMATE; EDETATE DISODIUM; .ALPHA.-TOCOPHEROL

Active Ingredient
Benzethonium Chloride 0.2%

Purpose
Antimicrobial

INDICATIONS AND USAGE

Keep your hands clean and germ-free everywhere you go!

WARNING:
For external use only.Not use around/in the eyes. In case of contact, flush thoroughly with water.

Stop use and ask a doctor if irritation and redness develop.

Keep out of reach of children.

DIRECTIONS:
Use wet wipe to clean hand without soap or water.

Inactive Ingredient

Water, Glycerin, Propylene Glycol, Aloe Barbadensis Leaf Juice, PEG-40 Hydrogenated Castor Oil, Iodopropynyl Butylcarbamate, Fragrance, Disodium EDTA, Vitamin E